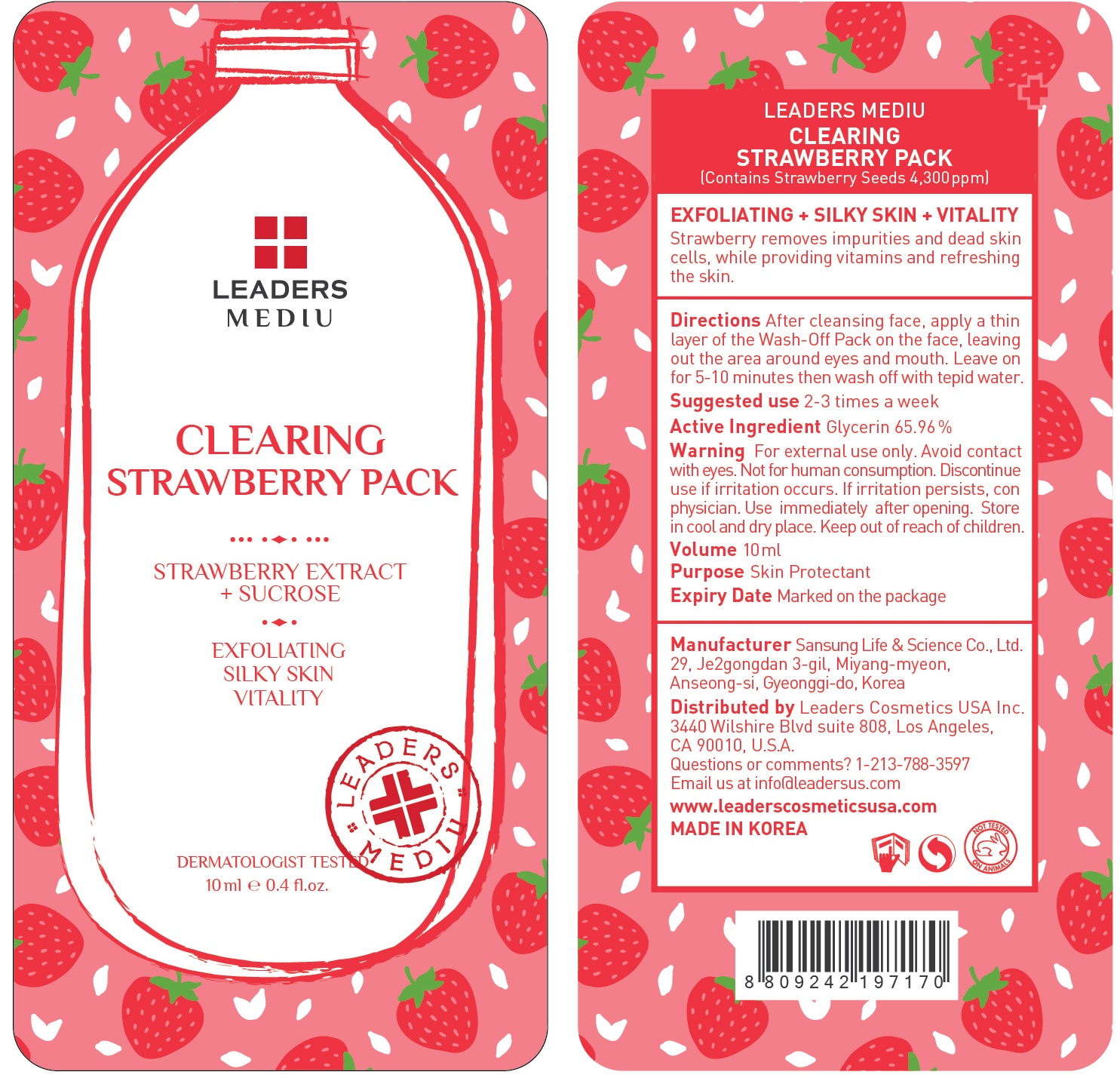 DRUG LABEL: Leaders Mediu Clearing Strawberry Pack
NDC: 69424-460 | Form: GEL
Manufacturer: SANSUNG LIFE & SCIENCE CO., LTD.
Category: otc | Type: HUMAN OTC DRUG LABEL
Date: 20160201

ACTIVE INGREDIENTS: Glycerin 6.59 g/10 mL
INACTIVE INGREDIENTS: Butylene Glycol; Water

ACTIVE INGREDIENT

Active Ingredient: Glycerin 65.96%

INACTIVE INGREDIENT

Inactive Ingredients: Butylene Glycol, Water, Sucrose, Caprylic/Capric Triglyceride, Polysorbate 60, Fragaria vesca (strawberry) seed, Caprylyl Glycol, Ethylhexylglycerin, Hydroxyethyl Acrylate/Sodium Acryloyldimethyl Taurate Copolymer, Citrus paradisi (grapefruit) seed extract, PEG-60 hydrogenated castor oil, Fragrance, Rubus idaeus (raspberry) fruit extract, Rosa canina fruit extract, Cornus officinalis fruit extract, Malpighia emarginata (acerola) fruit extract, Schizandra chinensis fruit extract, Vaccinium macrocarpon (cranberry) fruit extract, Crataegus oxyacantha fruit extract, Fragaria chiloensis (strawberry) fruit extract, Lycium chinense fruit extract, Rubus coreanus fruit extract, Artemisia princeps extract, CI 17200, CI 19140, CI 15985

PURPOSE

Purpose: Skin Protectant

WARNINGS

Warnings: For external use only. Avoid contact with eyes. Not for human consumption. Discontinue use if irritation occurs. If irritation persists, consult a physician.

Use immediately after opening. Store in cool and dry place. Keep out of reach of children.

KEEP OUT OF REACH OF CHILDREN

Directions

Directions: After cleansing face, apply a thin layer of the Wash-Off Pack on the face, leaving out the area around eyes and mouth. Leave on for 5-10 minutes then wash off with tepid water. *Suggested use is 2-3 times a week

Directions

Directions: After cleansing face, apply a thin layer of the Wash-Off Pack on the face, leaving out the area around eyes and mouth. Leave on for 5-10 minutes then wash off with tepid water. *Suggested use is 2-3 times a week